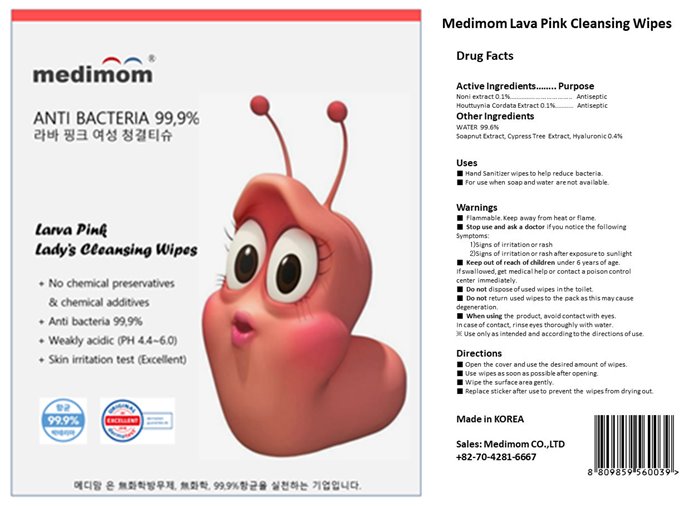 DRUG LABEL: Medimom Lava Pink Cleansing Wipes
NDC: 82380-103 | Form: LIQUID
Manufacturer: Medimom Inc.
Category: otc | Type: HUMAN OTC DRUG LABEL
Date: 20231211

ACTIVE INGREDIENTS: HOUTTUYNIA CORDATA FLOWERING TOP 0.1 g/100 g; MORINDA CITRIFOLIA LEAF 0.1 g/100 g
INACTIVE INGREDIENTS: CUPRESSUS SEMPERVIRENS LEAF OIL; SAPINDUS MUKOROSSI FRUIT; WATER; HYALURONIC ACID

82380

PURPOSE

antiseptic

Uses

■ Hand Sanitizer wipes to help reduce bacteria.

■ For use when soap and water are not available.

Active Ingredient

Noni extract 0.1%................................... Antiseptic

Houttuynia Cordata Extract 0.1%........... Antiseptic

Warnings

■ Flammable. Keep away from heat or flame.

Warnings

■ Keep out of reach of children under 6 years of age.

If swallowed, get medical help or contact a poison control

center immediately.

when using

■ When using the product, avoid contact with eyes.

In case of contact, rinse eyes thoroughly with water.

※ Use only as intended and according to the directions of use.

■ Stop use and ask a doctor if you notice the following

Symptoms:

1)Signs of irritation or rash
2)Signs of irritation or rash after exposure to sunlight

Warnings

■ Do not dispose of used wipes in the toilet.

■ Do not return used wipes to the pack as this may cause

degeneration.

Inactive Ingredients

WATER 99.6%

Soapnut Extract, Cypress Tree Extract, Hyaluronic 0.4%

directions

■ Open the cover and use the desired amount of wipes.

■ Use wipes as soon as possible after opening.

■ Wipe the surface area gently.

■ Replace sticker after use to prevent the wipes from drying out

label

82380-103-01